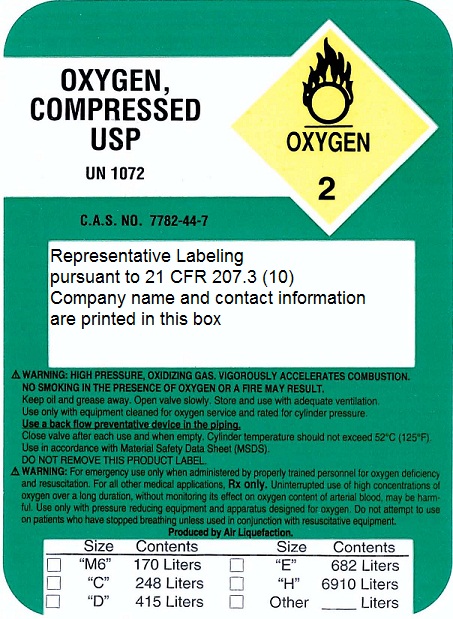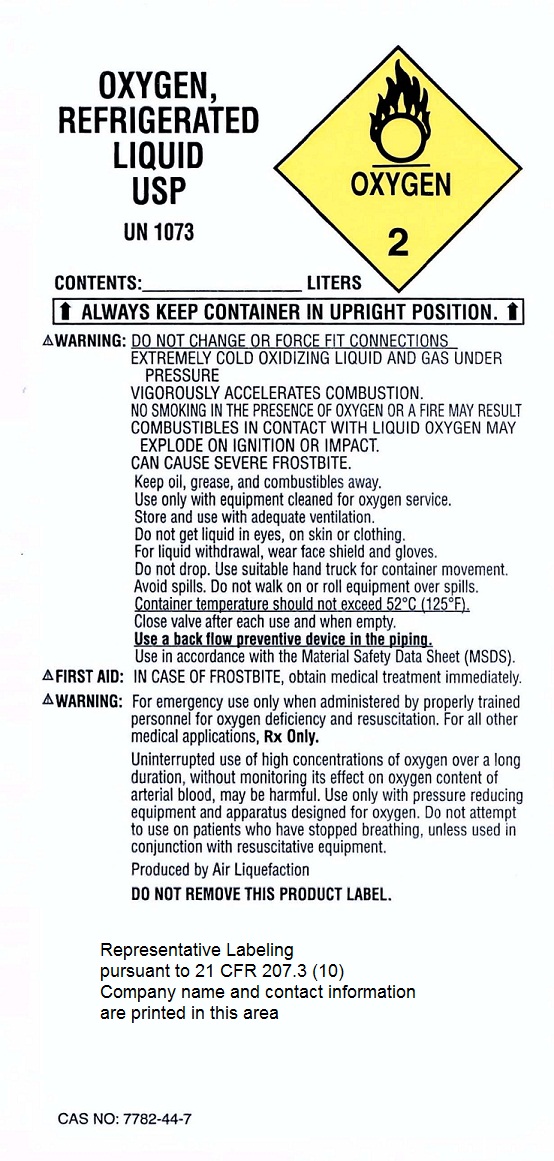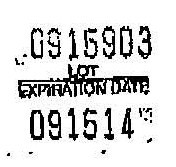 DRUG LABEL: Oxygen
NDC: 58142-7115 | Form: GAS
Manufacturer: St. John's Medical Supply
Category: prescription | Type: HUMAN PRESCRIPTION DRUG LABEL
Date: 20110103

ACTIVE INGREDIENTS: Oxygen 99 L/100 L

Oxygen